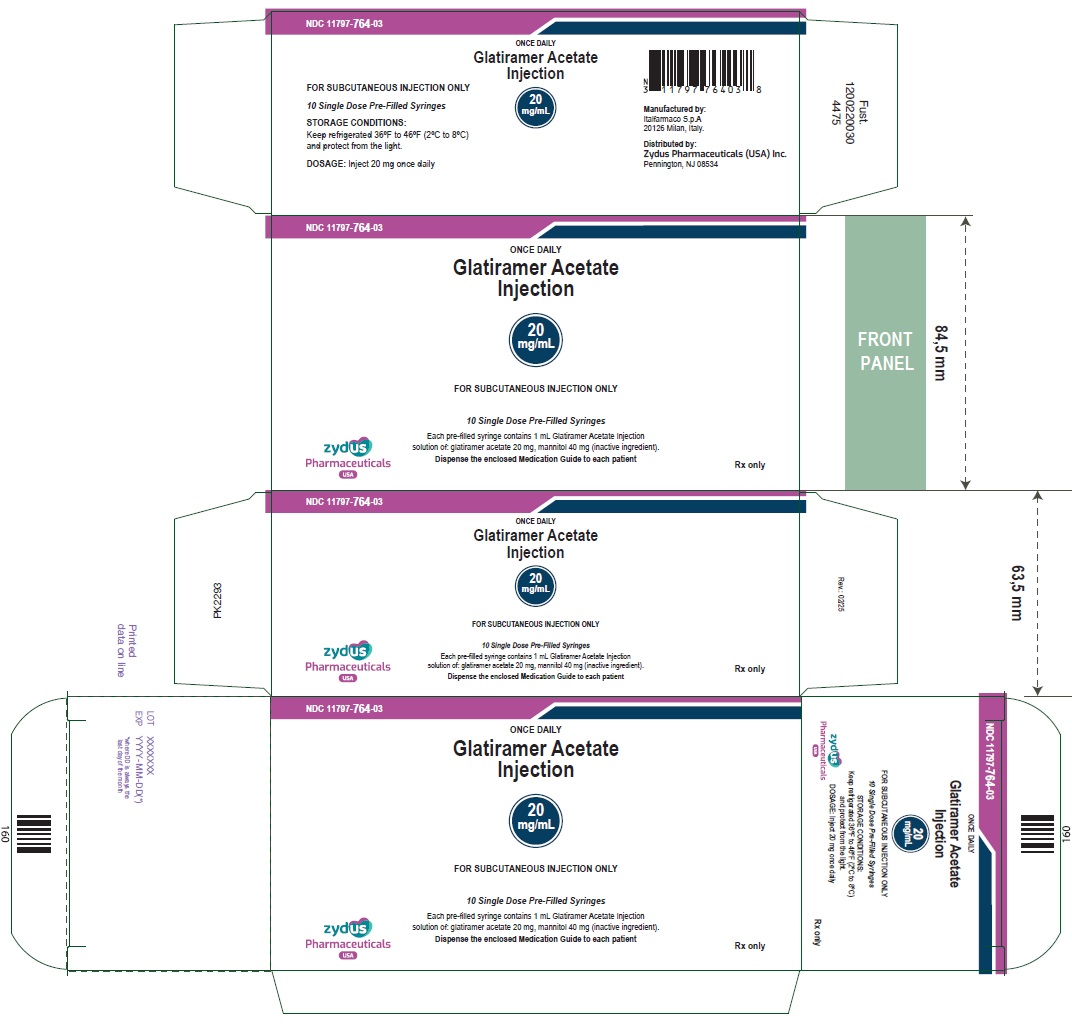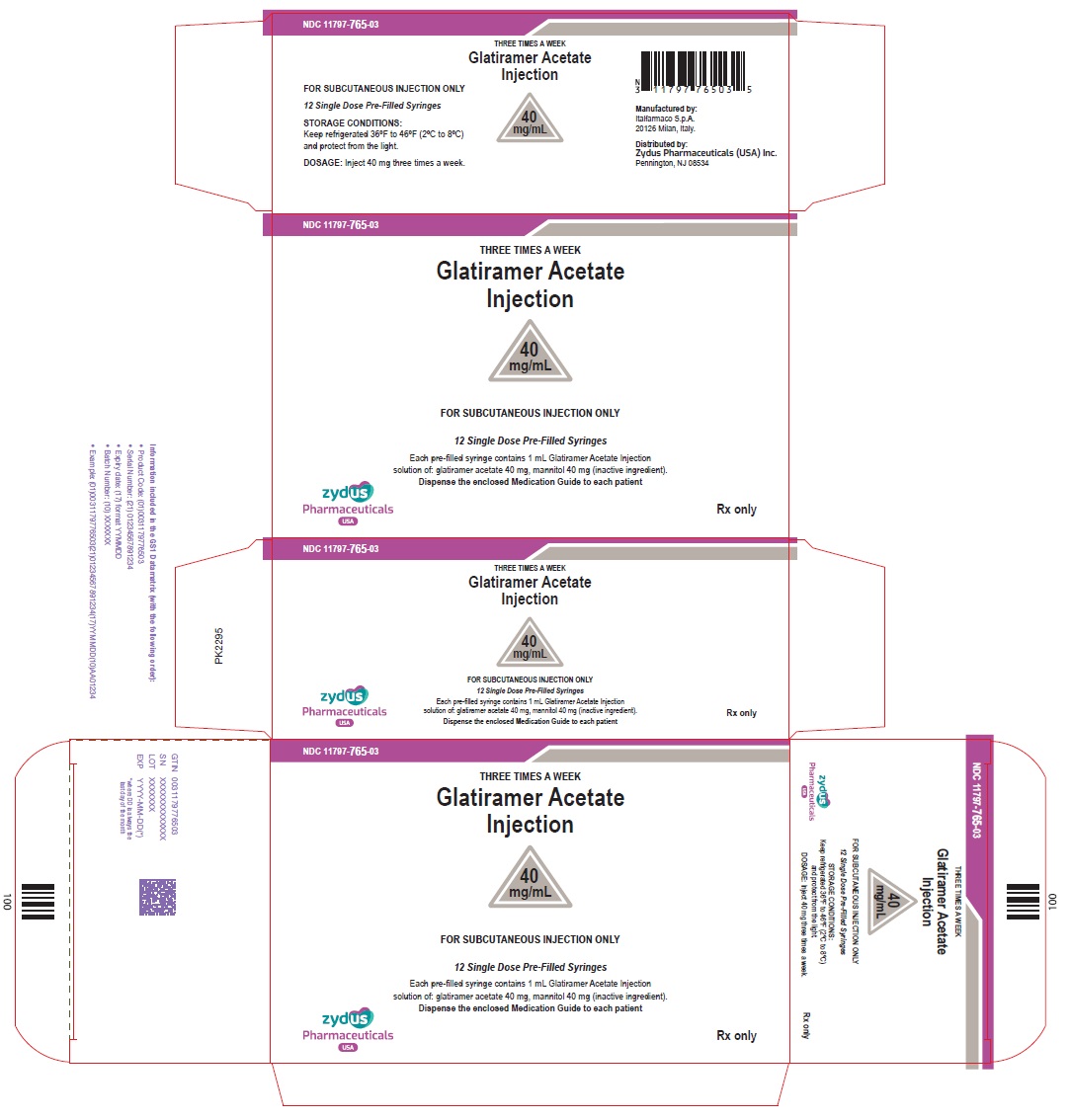 DRUG LABEL: GLATIRAMER ACETATE
NDC: 11797-764 | Form: INJECTION, SOLUTION
Manufacturer: Italfarmaco SpA
Category: prescription | Type: HUMAN PRESCRIPTION DRUG LABEL
Date: 20251031

ACTIVE INGREDIENTS: GLATIRAMER ACETATE 20 mg/1 mL
INACTIVE INGREDIENTS: MANNITOL 40 mg/1 mL; WATER

GLATIRAMER ACETATE injection, for subcutaneous use

PACKAGE LABEL.PRINCIPAL DISPLAY PANEL

NDC 11797-764-03

ONCE DAILY

Glatiramer Acetate
Injection

20
mg/mL

FOR SUBCUTANEOUS INJECTION ONLY

30 pre-filled syringe (3 carton box of 10 syringes)

Each pre-filled syringe contains 1 mL Glatiramer Acetate Injection
solution of: glatiramer acetate 20 mg, mannitol 40 mg (inactive ingredient).
Dispense the enclosed Medication Guide to each patient

zydus
Pharmaceuticals
USA

Rx only

NDC 11797-765-03

THREE TIMES A WEEK

Glatiramer Acetate
Injection

40
mg/mL

FOR SUBCUTANEOUS INJECTION ONLY

12 Single Dose Pre-Filled Syringes

Each pre-filled syringe contains 1 mL Glatiramer Acetate Injection
solution of: glatiramer acetate 40 mg, mannitol 40 mg (inactive ingredient).
Dispense the enclosed Medication Guide to each patient

zydus
Pharmaceuticals
USA

Rx only